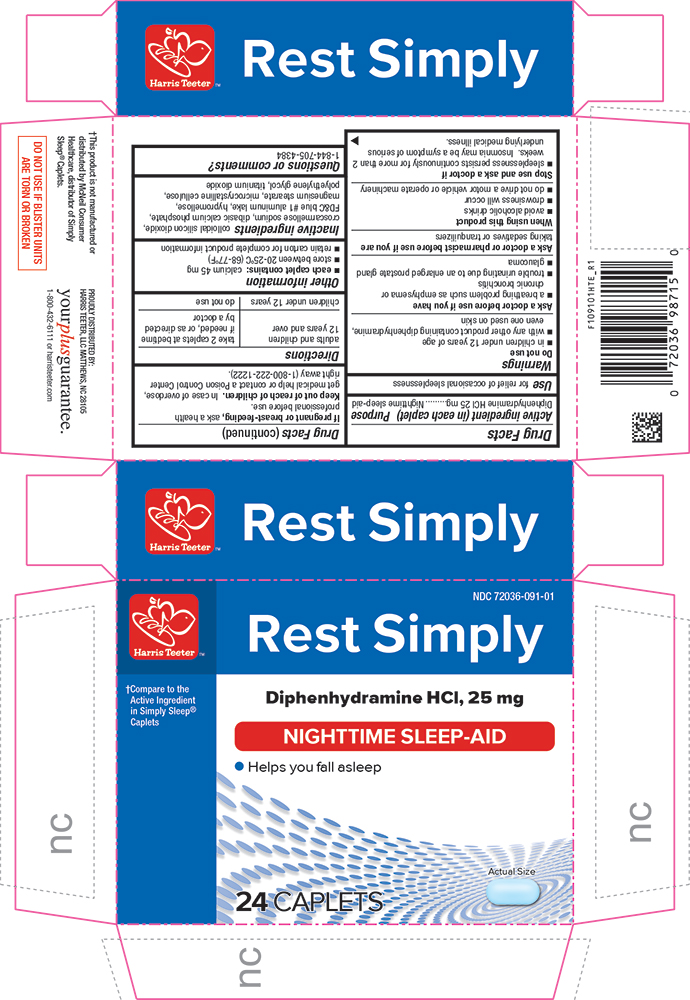 DRUG LABEL: Rest Simply
NDC: 72036-091 | Form: TABLET, COATED
Manufacturer: Harris Teeter
Category: otc | Type: HUMAN OTC DRUG LABEL
Date: 20250520

ACTIVE INGREDIENTS: DIPHENHYDRAMINE HYDROCHLORIDE 25 mg/1 1
INACTIVE INGREDIENTS: SILICON DIOXIDE; CROSCARMELLOSE SODIUM; CALCIUM PHOSPHATE, DIBASIC, ANHYDROUS; FD&C BLUE NO. 1; HYPROMELLOSE, UNSPECIFIED; MAGNESIUM STEARATE; CELLULOSE, MICROCRYSTALLINE; POLYETHYLENE GLYCOL, UNSPECIFIED; POLYSORBATE 80; TITANIUM DIOXIDE

HTE - 1091 - 2025-0520

Drug Facts

Active ingredient (in each caplet)

Diphenhydramine HCl 25 mg

Purpose

Nighttime sleep-aid

Use

for relief of occasional sleeplessness

Warnings

Do not use

- with any other product containing diphenhydramine, even one used on skin
- in children under 12 years of age

Ask a doctor before use if you have

- a breathing problem such as emphysema or chronic bronchitis
- trouble urinating due to an enlarged prostate gland
- glaucoma

Ask a doctor or pharmacist before use if you aretaking sedatives or tranquilizers

When using this productavoid alcoholic drinks

Stop use and ask a doctor ifsleeplessness persists continuously for more than 2 weeks. Insomnia may be a symptom of serious underlying medical illness.

PREGNANCY OR BREAST FEEDING

If pregnant or breast-feeding,ask a health professional before use.

Keep out of reach of children.In case of overdose, get medical help or contact a Poison Control Center right away.

Directions

adults and children 12 years of age and over | take 2 caplets at bedtime if needed, or as directed by a doctor
children under 12 years of age | do not use

Other information

- each caplet contains: calcium 45 mg
- store at room temperature 15°-30°C (59°-86°F)
- retain carton for complete product information

Inactive ingredients

colloidal silicon dioxide, croscarmellose sodium, dibasic calcium phosphate, FD&C blue #1, hypromellose, magnesium stearate, microcrystalline cellulose, polyethylene glycol, polysorbate 80, titanium dioxide

Questions or comments?

1-844-705-4384

PRINCIPAL DISPLAY PANEL

Harris Teeter™

NDC 72036-091-01

Rest Simply

†Compare to the Active Ingredient in Simply Sleep®

Diphenhydramine HCl, 25 mg

NIGHTTIME SLEEP-AID

• Helps you fall asleep

Actual Size

24 CAPLETS